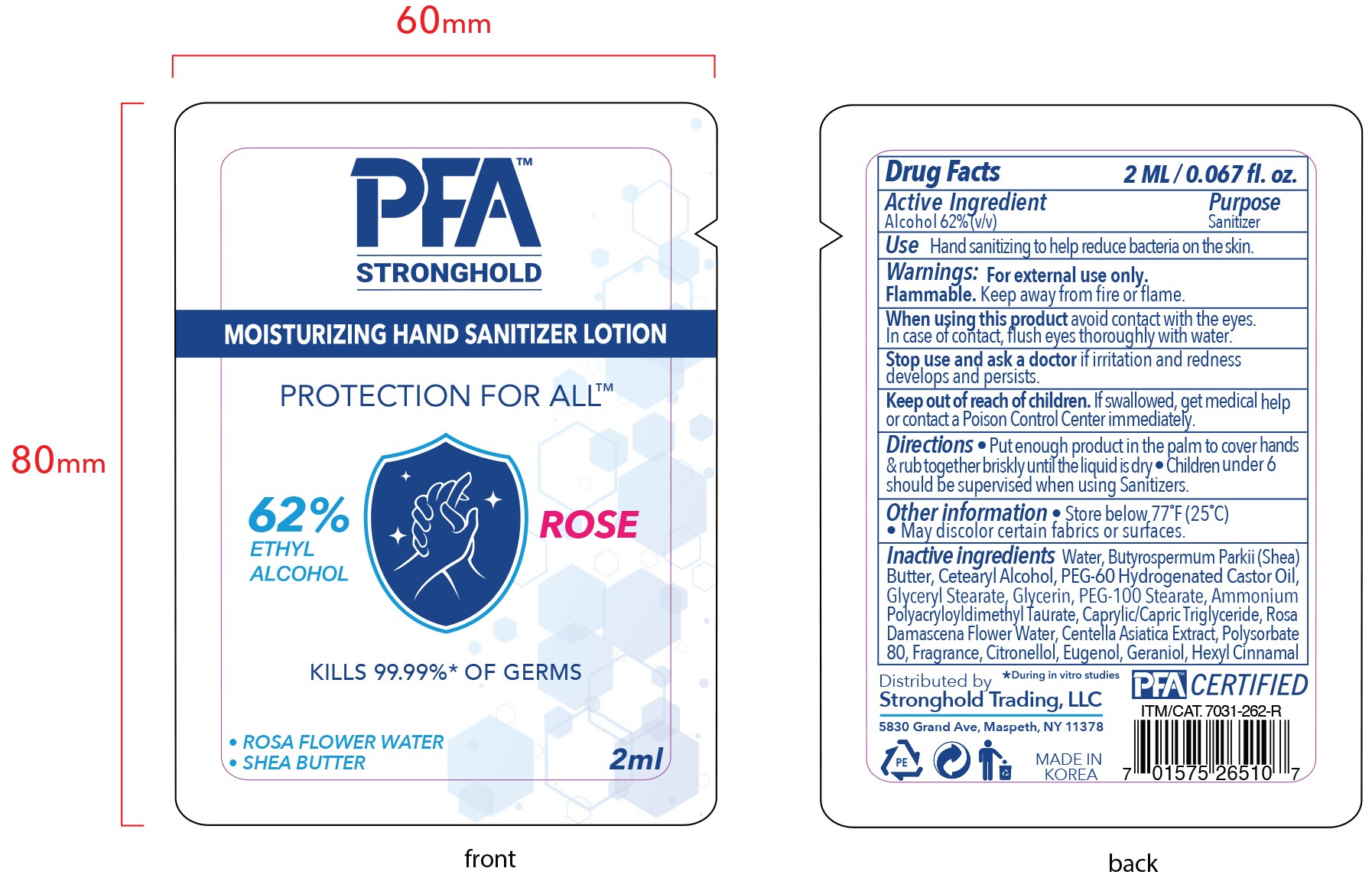 DRUG LABEL: PFA STRONGHOLD SANITIZING HANDLOTION ROSE
NDC: 80969-008 | Form: LOTION
Manufacturer: STRONGHOLD TRADING LLC
Category: otc | Type: HUMAN OTC DRUG LABEL
Date: 20230126

ACTIVE INGREDIENTS: ALCOHOL 62 mL/100 mL
INACTIVE INGREDIENTS: MEDIUM-CHAIN TRIGLYCERIDES; WATER; CETOSTEARYL ALCOHOL; POLYOXYL 60 HYDROGENATED CASTOR OIL; .ALPHA.-HEXYLCINNAMALDEHYDE; GERANIOL; EUGENOL; SHEA BUTTER; POLYSORBATE 80; .BETA.-CITRONELLOL, (R)-; ROSA DAMASCENA FLOWER OIL; GLYCERYL MONOSTEARATE; GLYCERIN; POLYOXYL 100 STEARATE; AMMONIUM POLYACRYLOYLDIMETHYL TAURATE (55000 MPA.S); CENTELLA ASIATICA TRITERPENOIDS

80969-008-01 PFA STRONGHOLD SANITIZING HAND LOTION_ROSE

Active ingredient

Alcohol 62%

Purpose

Sanitizer

Use

Hand sanitizing to help reduce bacteria on the skin.

Warnings

For external use only.

Flammable. Keep away from fire or flame.

When using this product

avoid contact with the eyes.

In case of contact, flush eyes thoroughly with water.

Stop use and ask a doctor

if irritation and redness develops and persists.

Keep out of reach of children.

If swallowed, get medical help or contact a Poison Control Center immediately.

Directions

- Put enough product in the palm to cover hands & rub together briskly the liquid is dry
- Children under 6 should be supervised when using Sanitizers.

Other information

- Store below 77°F (25°C)
- May discolor certain fabrics or surfaces.

Inactive ingredients

Water, Butyrospermum Parkii (Shea) Butter, Cetearyl Alcohol, PEG-60 Hydrogenated Castor Oil, Glyceryl Stearate, Glycerin, PEG-100 Stearate, Ammonium Polyacryloyldimethyl Taurate, Caprylic/Capric Triglyceride, Rosa Damascena Flower Water, Centella Asiatica Extract, Polysorbate 80, Fragrance, Citronellol, Eugenol, Geraniol, Hexyl Cinnamal